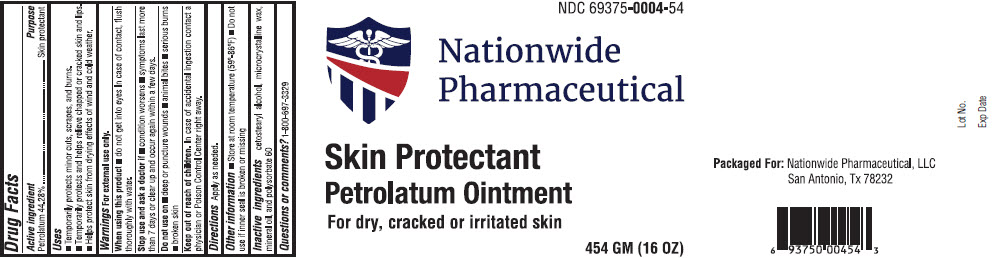 DRUG LABEL: SKIN PROTECTANT PETROLATUM
NDC: 69375-004 | Form: OINTMENT
Manufacturer: Nationwide Pharmaceutical, LLC
Category: otc | Type: HUMAN OTC DRUG LABEL
Date: 20210223

ACTIVE INGREDIENTS: Petrolatum 44.28 g/100 g
INACTIVE INGREDIENTS: MINERAL OIL; MICROCRYSTALLINE WAX; CETOSTEARYL ALCOHOL; POLYSORBATE 60

SKIN PROTECTANT PETROLATUM OINTMENT

Drug Facts

Active ingredient

Petrolatum 44.28%

Purpose

Skin protectant

Uses

- Temporarily protects minor cuts, scrapes, and burns.
- Temporarily protects and helps relieve chapped or cracked skin and lips.
- Helps protect skin from drying effects of wind and cold weather.

Warnings

For external use only.

When using this product

- do not get into eyes In case of contact, flush thoroughly with water.

Stop use and ask a doctor if

- condition worsens
- symptoms last more than 7 days or clear up and occur again within a few days.

Do not use on

- deep or puncture wounds
- animal bites
- serious burns
- broken skin

Keep out of reach of children. In case of accidental ingestion contact a physician or Poison Control Center right away.

Directions

Apply as needed.

Other information

- Store at room temperature (59°-86°F)
- Do not use if inner seal is broken or missing

Inactive ingredients

cetostearyl alcohol, microcrystalline wax, mineral oil, and polysorbate 60

Questions or comments?

1-800-697-3329

PRINCIPAL DISPLAY PANEL - 454 GM Jar Label

NDC 69375-0004-54

Nationwide
Pharmaceutical

Skin Protectant
Petrolatum Ointment

For dry, cracked or irritated skin

454 GM (16 OZ)